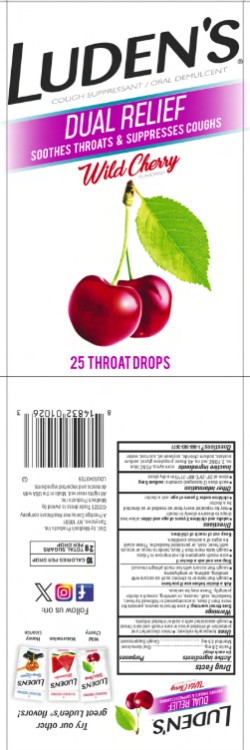 DRUG LABEL: Ludens
NDC: 52183-227 | Form: LOZENGE
Manufacturer: Prestige Brands Holdings, Inc.
Category: otc | Type: HUMAN OTC DRUG LABEL
Date: 20251023

ACTIVE INGREDIENTS: PECTIN 2.8 mg/1 1; MENTHOL 2.5 mg/1 1
INACTIVE INGREDIENTS: CORN SYRUP; FD&C BLUE NO. 2; FD&C RED NO. 40; PROPYLENE GLYCOL; SODIUM ACETATE; SODIUM CHLORIDE; SOYBEAN OIL; SUCROSE; WATER

Ludens Dual Relief Wild Cherry - 52183-227-25

Drug Facts

Active ingredient (in each drop)

Pectin 2.8 mg

Menthol 2.5 mg

Purpose

Oral demulcent

Cough suppressant

Uses

temporarily relieves:

- minor discomfort and protection of irritated areas in sore mouth and sore throat
- cough associated with a cold or inhaled irritants.

Warnings

Sore throat warning: if sore throat is severe, persists for more than 2 days, is accompanied or followed by fever, headache, rash, nausea, or vomiting, consult a doctor promptly. These may be serious.

Ask a doctor before use if you have

- cough that lasts or is chronic such as occurs with smoking, asthma, or emphysema
- cough that occurs with too much phlegm (mucus)

Stop use and ask a doctor if

- sore mouth symptoms do not improve in 7 days
- cough lasts more than 7 days, tends to recur, or occurs with fever, rash, or persistent headache. These could be signs of a serious condition.

Directions

- adults and children 3 years of age and older: allow two drops to dissolve slowly in mouth
- may be repeated as needed or as directed by a doctor
- children under 3 years of age: ask a doctor

Other information

- each dose (2 lozenges) contains: sodium 5 mg
- store at 20º-25ºC (68º-77ºF) in a dry place

Inactive ingredients

corn syrup, FD&C blue no. 2, FD&C red no. 40, flavor, propylene glycol, sodium acetate, sodium chloride, soybean oil, sucrose, water

Questions?

1-866-583-3677 Ludens.com

Distributed by Medtech Products Inc.
Tarrytown, NY 10591
A Prestige Brands Company
© 2025 Trade dress is owned by Medtech Products Inc. All rights reserved.

PRINCIPAL DISPLAY PANEL

Luden’s®

Cough Suppressant/Oral Demulcent

DUAL RELIEF

Wild Cherry

25 Cough Drops